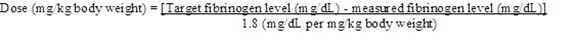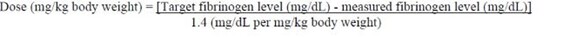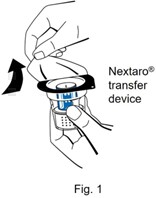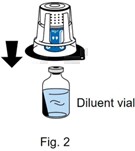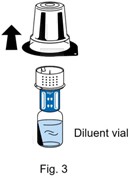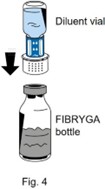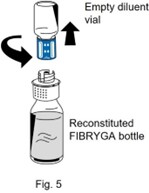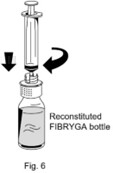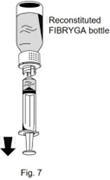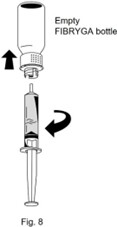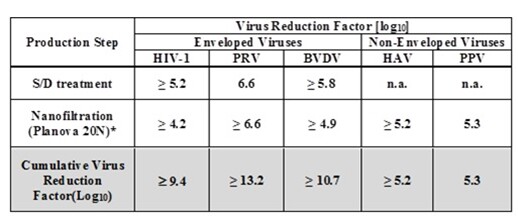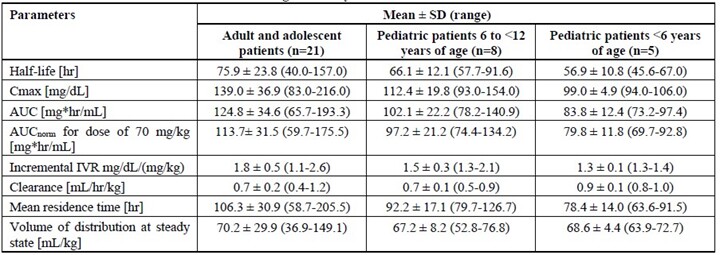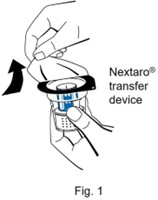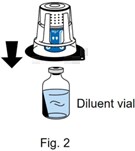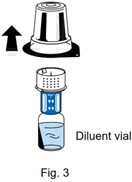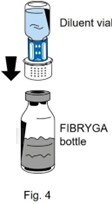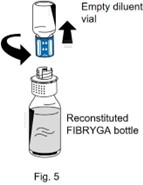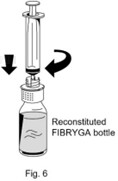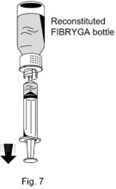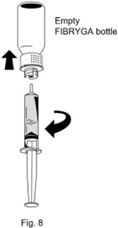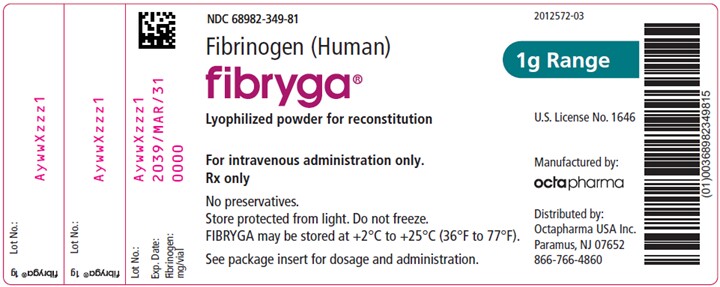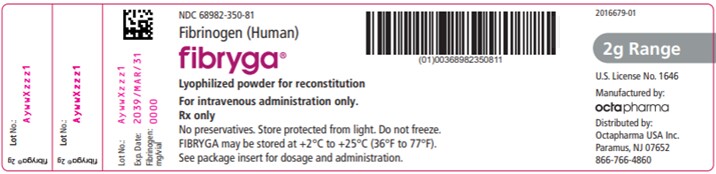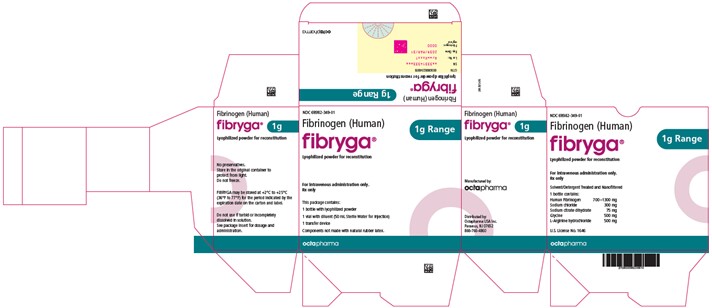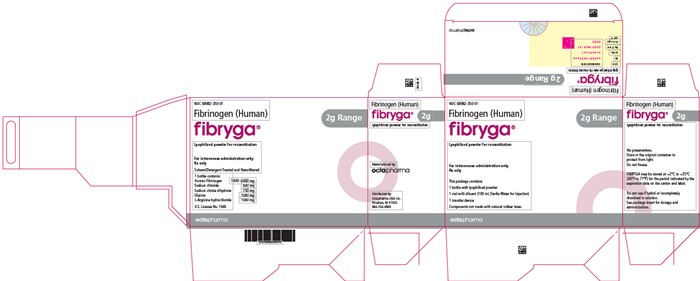 DRUG LABEL: Fibryga
NDC: 68982-350 | Form: POWDER, FOR SOLUTION
Manufacturer: Octapharma USA Inc
Category: other | Type: PLASMA DERIVATIVE
Date: 20250805

ACTIVE INGREDIENTS: FIBRINOGEN HUMAN 20 mg/1 mL

HIGHLIGHTS OF PRESCRIBING INFORMATION

These highlights do not include all the information needed to use FIBRYGA safely and effectively. See full prescribing information for FIBRYGA.
FIBRYGA® [fibrinogen (human)]
Lyophilized Powder for Reconstitution, For Intravenous Use
Initial U.S. Approval: 2017

RECENT MAJOR CHANGES

Indications and Usage (1) 07/2024

Dosage and Administration, Dosage (2.1) 07/2024

Dosage and Administration, Administration (2.3) 07/2024

Dosage and Administration, Preparation and Handling (2.2) 08/2024

Dosage and Administration, Administration (2.3) 08/2024

1 INDICATIONS AND USAGE

FIBRYGA is a human fibrinogen concentrate indicated for:

fibrinogen supplementation in bleeding patients with acquired fibrinogen deficiency

treatment of acute bleeding episodes in patients with congenital fibrinogen deficiency, including afibrinogenemia and hypofibrinogenemia (1).

Limitations of Use:

FIBRYGA is not indicated for dysfibrinogenemia (1).

2 DOSAGE AND ADMINISTRATION

For intravenous use after reconstitution only. (2 .1)

Acquired Fibrinogen Deficiency

Recommended dose (2.1)

For adults: 4g

For adolescents age ≥ 12 years: 50 mg/kg body weight

For children age <12 years: 70 mg/kg body weight

Administer additional doses as needed to bleeding patients when plasma fibrinogen level is ≤200 mg/dL or thromboelastometry FIBTEM A10 is ≤10 mm (or equivalent values generated by other viscoelastic testing methods) (2.1).

Dosing may be adjusted depending on plasma fibrinogen levels or viscoelastic testing, severity of bleeding, body weight, or patient’s clinical condition (2.1).

The injection rate should not exceed 20 mL per minute (2.3).

Monitoring of patient’s plasma fibrinogen level or the viscoelastic properties of the fibrin-based clot is recommended during treatment (2.1).

Congenital Fibrinogen Deficiency

Dose when plasma fibrinogen level is known (2.1):

Adults and adolescents 12 years of age and above:

Dose (mg/kg body weight) =

[Target fibrinogen level (mg/dL) - measured fibrinogen level (mg/dL)]

1.8 (mg/dL per mg/kg body weight)

Children <12 years of age:

Dose (mg/kg body weight) =

[Target fibrinogen level (mg/dL) - measured fibrinogen level (mg/dL)]

1.4 (mg/dL per mg/kg body weight)

The recommended target plasma fibrinogen level is 100 mg/dL for minor bleeding and 150 mg/dL for major bleeding.

Dose when plasma fibrinogen level is unknown: 70 mg/kg body weight (2.1).

The injection rate should not exceed 5 mL per minute (2.3).

Monitoring of patient’s plasma fibrinogen level is recommended during treatment.

3 DOSAGE FORMS AND STRENGTHS

FIBRYGA is available as a lyophilized powder for reconstitution for intravenous use in a single-dose bottle containing approximately 1 g fibrinogen in 50 mL reconstitution volume or 2 g fibrinogen in 100 mL reconstitution volume (3).

4 CONTRAINDICATIONS

Anaphylactic or severe reactions to FIBRYGA or its components (Sodium Citrate Dihydrate; Glycine; L-Arginine Hydrochloride) (4).

5 WARNINGS AND PRECAUTIONS

Monitor patients for early signs of hypersensitivity or allergic reactions. If necessary, discontinue administration and institute appropriate treatment (5.1).

Thrombotic events have been reported in patients receiving FIBRYGA. Treatment with human fibrinogen concentrate in congenital fibrinogen deficiency has been associated with thrombosis at target plasma fibrinogen levels that were below 150 mg/dL. The thrombotic risks may be greater when the target fibrinogen plasma level is 150 mg/dL. Weigh the benefits of administration versus the risks of thrombosis (5.2).

FIBRYGA is made from pooled human plasma. Products made from human plasma may contain infectious agents, e.g., viruses and, theoretically, the Creutzfeldt-Jakob disease (CJD) agent (5.3).

6 ADVERSE REACTIONS

The most serious adverse reactions that may be observed with FIBRYGA are thromboembolic episodes and anaphylactic-type reactions.

The most common adverse reactions observed in clinical studies with FIBRYGA in acquired fibrinogen deficiency (> 5% of patients) were abnormal hepatic function, acute kidney injury, anemia, atrial fibrillation, delirium and renal failure (6).

The most common adverse reactions observed in clinical studies with FIBRYGA in congenital fibrinogen deficiency (> 5% of patients) were nausea, vomiting, pyrexia (fever), and thrombocytosis (6).

To report SUSPECTED ADVERSE REACTIONS, contact Octapharma at 1-866-766-4860 or FDA at 1-800-FDA-1088 or www.fda.gov/medwatch.

8 USE IN SPECIFIC POPULATIONS

Pediatric: There was no difference in the pharmacokinetics of FIBRYGA between adults and adolescents (12-17 years of age). Lower recovery, shorter half-life and faster clearance were observed in children aged 1 to < 12 years; higher doses may be required in this age group in patients with acquired or congenital fibrinogen deficiency (8.4).

FULL PRESCRIBING INFORMATION

1 INDICATIONS AND USAGE

1.1 Acquired Fibrinogen Deficiency

FIBRYGA is indicated for fibrinogen supplementation in bleeding patients with acquired fibrinogen deficiency.

1.2 Congenital Fibrinogen Deficiency

FIBRYGA is indicated for the treatment of acute bleeding episodes in patients with congenital fibrinogen deficiency, including afibrinogenemia and hypofibrinogenemia.

Limitations of Use:

FIBRYGA is not indicated for dysfibrinogenemia.

2 DOSAGE AND ADMINISTRATION

2.1 Dosage

For intravenous use after reconstitution only.

Acquired Fibrinogen Deficiency:

The recommended dose is as follows:

- For adults: 4g
- For adolescents age ≥ 12 years: 50 mg/kg body weight
- For children age <12 years: 70 mg/kg body weight

Administer additional doses of 4 g in adults, 50 mg/kg body weight in adolescents 12 years of age and above, and 70 mg/kg body weight in children <12 years of age as needed to bleeding patients when plasma fibrinogen level is ≤200 mg/dL or thromboelastometry FIBTEM A10 is ≤10 mm (or equivalent values generated by other viscoelastic testing methods). Dosing may be adjusted depending on plasma fibrinogen levels or viscoelastic testing, severity of bleeding, body weight, or patient’s clinical condition.

Monitor the patient’s plasma fibrinogen level or the viscoelastic properties of the fibrin-based clot during treatment with FIBRYGA.

Congenital Fibrinogen Deficiency:

FIBRYGA dosing, duration of dosing, and frequency of administration should be individualized based on the extent of bleeding, laboratory values, and the clinical condition of the patient.

The recommended target plasma fibrinogen level is 100 mg/dL for minor bleeding and 150 mg/dL for major bleeding.

FIBRYGA dose when baseline fibrinogen level is known

Dose should be individually calculated for each patient based on the target plasma fibrinogen level for the type of bleeding, actual measured plasma fibrinogen level and body weight , using the following age-specific formulas [see Clinical pharmacology (12.3)] :

Adults and adolescents 12 years of age and above:

Children <12 years of age:

FIBRYGA dose when baseline fibrinogen level is not known

If the patient’s fibrinogen level is not known, the recommended dose is 70 mg/kg of body weight administered intravenously.

Monitor the patient’s fibrinogen level during treatment with FIBRYGA.

Additional infusions of FIBRYGA should be administered if the plasma fibrinogen level is below the accepted lower limit (80 mg/dL for minor bleeding, 130 mg/dL for major bleeding) of the target level until hemostasis is achieved.

2.2 Preparation and Handling

FIBRYGA package contains:

- 1 single-dose bottle of FIBRYGA concentrate
- 1 vial of diluent (sterile Water for Injection)
- 1 transfer device (Nextaro ®)

Reconstitute FIBRYGA with diluent (sterile Water for Injection).

Do not use FIBRYGA beyond the expiration date. FIBRYGA contains no preservatives. Use aseptic technique when preparing and reconstituting FIBRYGA.

The procedures below are provided as general guidelines for preparation and reconstitution of FIBRYGA.

Reconstitute FIBRYGA as follows:

1. Warm both the powder and sterile Water for Injection (sWFI) in their closed bottles to room temperature. This temperature should be maintained during reconstitution. If a water bath is used for warming, prevent water from coming into contact with the rubber stoppers or the caps of the bottles. The temperature of the water bath should not exceed +37°C (98°F).
2. Remove the flip cap from the FIBRYGA bottle and the sWFI vial and disinfect the rubber stoppers with an alcohol swab and allow to dry.
3. Open the Nextaro ® transfer device package by peeling off the lid (Fig. 1). To maintain sterility, do not remove the Nextaro ® transfer device from the blister package. Do not touch the spike.

4. Place the diluent vial on an even, clean surface and hold it firmly. Without removing the blister package, place the blue part of the transfer device on top of the diluent vial. Press straight and firmly down until it snaps into place (Fig. 2). Do not twist while attaching.
Note:
The transfer device must be attached to the diluent vial first and then to the lyophilized powder bottle. Otherwise, loss of vacuum occurs, and transfer of the diluent does not take place. If diluent is not completely transferred to the lyophilized powder bottle during this process, contact your Octapharma representative.

5. While holding onto the diluent vial, carefully remove the blister package from the Nextaro ® transfer device by pulling vertically upwards. Make sure to leave the transfer device attached firmly to the diluent vial (Fig. 3).

6. Place the FIBRYGA bottle on an even, clean surface and hold it firmly. Take the diluent vial with the attached transfer device and turn it upside down. Place the white part of the transfer device connector on top of the FIBRYGA bottle and press firmly down until it snaps into place (Fig. 4). Do not twist while attaching. The diluent will flow automatically into the FIBRYGA bottle.

7. With the diluent vial still attached, gently swirl the FIBRYGA bottle until the powder is fully dissolved. To avoid foam formation, do not shake the bottle. The powder should be dissolved completely within approximately 5-10 minutes. Unscrew the Nextaro ® transfer device (blue part) counterclockwise into two parts (Fig. 5). Do not touch the Luer lock connector on the white part of the transfer device.
8. Dispose of the empty diluent vial together with the blue part of the transfer device.

- After reconstitution, the FIBRYGA solution should be almost colorless and slightly opalescent. Inspect the reconstituted FIBRYGA solution in the syringe for visible particulate matter and discoloration prior to administration. Do not use if particulate matter or discoloration are observed.

The powder should be reconstituted only directly before injection. After reconstitution, do not refrigerate or freeze the FIBRYGA solution. Use the reconstituted FIBRYGA solution immediately or within 4 hours after reconstitution. Discard any remaining FIBRYGA solution.

2.3 Administration

For intravenous use only after reconstitution.

Instructions for infusion:

1. Carefully attach a syringe to the Luer lock connector on the white part of the Nextaro ® transfer device (Fig. 6).

2. Turn the FIBRYGA bottle upside down and draw the solution into the syringe (Fig. 7).

3. Once the solution has been transferred, firmly hold the barrel of the syringe (keeping the syringe plunger facing down) and remove the syringe from the Nextaro ® transfer device (Fig. 8).
4. Dispose of the white part of the transfer device together with the empty FIBRYGA bottle.

- Do not administer FIBRYGA in the same tubing or container as other medications.
- Use aseptic technique when administering FIBRYGA.
- Administer FIBRYGA at room temperature by slow intravenous injection at a rate not exceeding 20 mL per minute in patients with acquired fibrinogen deficiency and 5 mL per minute in patients with congenital fibrinogen deficiency.
- Flush infusion line with normal saline before and after administration of FIBRYGA.
- No blood should enter the syringe due to the risk of fibrin clot formation.

3 DOSAGE FORMS AND STRENGTHS

FIBRYGA is a sterile, lyophilized powder for reconstitution for intravenous use. FIBRYGA is provided in a single-dose bottle containing approximately 1 g fibrinogen in 50 mL reconstitution volume or 2 g fibrinogen in 100 mL reconstitution volume.

4 CONTRAINDICATIONS

FIBRYGA is contraindicated in individuals who have manifested severe immediate hypersensitivity reactions, including anaphylaxis, to FIBRYGA or its components (Sodium Citrate Dihydrate; Glycine; L-Arginine Hydrochloride).

5 WARNINGS AND PRECAUTIONS

5.1 Hypersensitivity Reactions

Hypersensitivity reactions may occur. If early signs of hypersensitivity reactions (including hives, generalized urticaria, tightness of the chest, wheezing, hypotension, and anaphylaxis) or symptoms of allergic reactions occur, immediately discontinue administration [see Patient Counseling Information (17)] . The treatment required depends on the nature and severity of the reaction.

5.2 Thrombosis

Thrombosis may occur spontaneously in patients with acquired or congenital fibrinogen deficiency with or without the use of fibrinogen replacement therapy. Thrombotic events have been reported in patients receiving FIBRYGA.

In the FIBRES study, there were 32 patients (8.6%) in the FIBRYGA group who experienced a total of 37 thromboembolic adverse events: cerebrovascular accident (n=17 events); intestinal ischemia (n=4); deep vein thrombosis (n=3); myocardial infarction (n=3); peripheral ischemia (n=2); pulmonary embolism (n=3); transient ischemic attack (n=1); cardiac arrest (n=1); disseminated intravascular coagulation (n=1); ischemic hepatitis (n=1); and thrombophlebitis (n=1). In the cryoprecipitate group, 45 patients (12.4%) experienced a total of 50 thromboembolic adverse events: cerebrovascular accident (n =18 events); venous thrombosis (n=13); cardiac arrest (n=4); myocardial infarction (n=4); intestinal ischemia (n=3); transient ischemic attack (n=1); amaurosis fugax (n=1); aortic thrombosis (n=1); medullar ischemia (n=1); optic ischemic neuropathy (n=1); peripheral artery occlusion (n=1); peripheral ischemia (n=1); and vascular graft occlusion (n=1).

Treatment with human fibrinogen concentrate in congenital fibrinogen deficiency has been associated with risk of thrombosis at target fibrinogen levels that were less than 150 mg/dL. The risk of thrombosis may be greater when the target fibrinogen plasma level is 150 mg/dL. Weigh the benefits of FIBRYGA administration versus the risks of thrombosis. Patients receiving FIBRYGA should be monitored for signs and symptoms of thrombosis. [see Patient Counseling Information (17)]

5.3 Transmissible Infectious Agents

FIBRYGA is made from human plasma. Products made from human plasma may contain infectious agents (e.g., viruses and the CJD agent that can cause disease). Also, unknown infectious agents may be present in such products [see Patient Counseling Information (17)] . The risk that such products will transmit an infectious agent has been reduced by screening plasma donors for prior exposure to certain viruses, by testing for the presence of certain current virus infections, and by a process demonstrated to inactivate and/or remove certain viruses during manufacturing [see Description (11)] . Despite these measures, such products may transmit disease. All infections thought by a physician possibly to have been transmitted by this product should be reported by the physician or other healthcare provider to Octapharma at 1-866-766-4860.

6 ADVERSE REACTIONS

6.1 Clinical Trials Experience

Because clinical trials are conducted under widely varying conditions, adverse reaction rates observed in the clinical trials of a drug cannot be directly compared to the rate in the clinical trials of another drug and may not reflect the rates observed in practice.

Four hundred twenty-eight patients received at least one dose of FIBRYGA for the treatment of bleeding and/or for perioperative management. In total, 677 doses were infused in five studies.

The safety of FIBRYGA was investigated in FIBRES, a randomized controlled trial comparing FIBRYGA to cryoprecipitate in adult patients with acquired fibrinogen deficiency who were experiencing clinically significant bleeding and hypofibrinogenemia after cardiac surgery. In total, 1296 adverse events occurred in 512 patients during the study after receipt of fibrinogen supplementation: 623 events in 248 (66.7%) patients in the FIBRYGA group, and 673 events in 264 (72.7%) patients in the cryoprecipitate group.

A total of 35 (9.41%) patients died in the period up to postoperative day 28 in the FIBRYGA group and 27 (7.44%) patients died in the cryoprecipitate group. After postoperative day 28, an additional 5 patients died after receiving FIBRYGA and an additional 2 patients died after receiving cryoprecipitate.

Serious adverse reactions occurred in 117 (31.5%) patients in the FIBRYGA group compared to 126 (34.7%) patients in the cryoprecipitate group.

The most common adverse reactions are shown in Table 1.

Table 1: Adverse Reactions Reported in More Than 5% of Patients Following FIBRYGA or Cryoprecipitate Administration in the FIBRES Study

 | FIBRYGA Patients (N=372) n (%) | Cryoprecipitate Patients (N=363) n (%)
Cardiac disorders
Atrial fibrillation | 108 (29.0%) | 122 (33.6%)
Blood and lymphatic system disorders
Anemia | 58 (15.6%) | 52 (14.3%)
Thrombocytopenia | 15 (4.0%) | 20 (5.5%)
Psychiatric disorders
Delirium | 56 (15.1%) | 54 (14.9%)
Renal and urinary disorders
Acute kidney injury | 29 (7.8%) | 29 (8.0%)
Renal failure | 19 (5.1%) | 19 (5.2%)
Hepatobiliary disorders
Hepatic function abnormal | 27 (7.3%) | 26 (7.2%)
Infections and infestations
Pneumonia | 18 (4.8%) | 19 (5.2%)

In the congenital fibrinogen deficiency studies, one patient had a mild skin reaction (itchiness and redness) after FIBRYGA administration for a bleeding episode and was treated with diphenhydramine and hydrocortisone. Thereafter, the patient received another infusion of FIBRYGA for the treatment of the same bleeding episode and another FIBRYGA infusion for surgical management during the next week. For both of those FIBRYGA infusions the patient was treated with diphenhydramine and hydrocortisone prophylactically and did not experience any drug reactions.

Further adverse reactions included one case each of digital foot ischemia, portal vein thrombosis following splenectomy, and peripheral phlebitis of the upper limbs.

The following serious adverse reactions are described elsewhere in the labeling:

- Hypersensitivity reactions [see Warnings and Precautions (5.1)]
- Thrombosis risk [see Warning and Precautions (5.2)]
- Possible transmission of infectious agents [see Warnings and Precautions (5.3)]

8 USE IN SPECIFIC POPULATIONS

8.1 Pregnancy

Risk Summary

There are no data with FIBRYGA use in pregnant women to determine whether there is a drug-associated risk. Animal reproduction studies have not been conducted with FIBRYGA. It is not known whether FIBRYGA can cause fetal harm when administered to a pregnant woman or can affect fertility. In the U.S. general population, the estimated background risk of major birth defects and miscarriage in clinically recognized pregnancies is 2-4% and 15-20%, respectively.

8.2 Lactation

Risk Summary

There is no information regarding the presence of FIBRYGA in human milk, the effect on the breastfed infant, or the effects on milk production. The developmental and health benefits of breastfeeding should be considered along with the mother’s clinical need for FIBRYGA and any potential adverse effects on the breastfed infant from FIBRYGA or from the underlying maternal condition.

8.4 Pediatric Use

The safety and effectiveness of FIBRYGA have been established in pediatric patients for fibrinogen supplementation in acquired and congenital fibrinogen deficiency. Use of FIBRYGA is supported by evidence from adequate and well-controlled studies in adults with acquired fibrinogen deficiency and safety data in pediatric patients in congenital fibrinogen deficiency [see Clinical Studies (14)].

Pharmacokinetic studies were only performed in patients with congenital fibrinogen deficiency. There was no difference in the pharmacokinetics of FIBRYGA between adults and adolescents.

Lower incremental in vivo recovery (IVR), faster clearance and shorter half-life were observed in children aged 1 to < 12 years, compared to adults and adolescents. As higher doses of FIBRYGA were administered for the treatment of bleeding episodes in children aged 1 to < 12 years, higher doses may be required in this age group in patients with acquired or congenital fibrinogen deficiency [see Dosage and Administration (2.1)].

8.5 Geriatric Use

A total of 177 patients >65 years were treated with FIBRYGA in clinical studies in acquired fibrinogen deficiency, representing 47.6% of the patients in the FIBRYGA group.

Clinical studies of FIBRYGA in congenital fibrinogen deficiency did not include sufficient numbers of patients aged 65 years and over to provide conclusive evidence as to whether or not they respond differently than younger patients.

11 DESCRIPTION

FIBRYGA [fibrinogen (human)] is a human plasma-derived, sterile, purified, virus-inactivated and nanofiltered (20 nm) fibrinogen concentrate.

FIBRYGA is supplied as a lyophilized powder, white or pale yellow in color, for reconstitution for intravenous use. FIBRYGA contains no preservatives. Each bottle contains approximately 1 g or 2 g of fibrinogen. The actual potency of fibrinogen in mg is stated on each FIBRYGA carton and bottle. The diluent for reconstitution of the lyophilized powder is 50 mL (1 g) or 100 mL (2 g) sterile Water for Injection.

The nominal composition of FIBRYGA is as follows:

Component | Quantity/ mL
Human Fibrinogen | 20 mg
Sodium Chloride | 6 mg
Sodium Citrate Dihydrate | 1.5 mg
Glycine | 10 mg
L-Arginine Hydrochloride | 10 mg

All units of human plasma used in the manufacture of FIBRYGA are provided by FDA-approved blood establishments, and are tested by FDA-licensed serological tests for Hepatitis B surface antigen (HBsAg), antibodies to Hepatitis C Virus (HCV) and Human Immunodeficiency Virus (HIV)-1/2. As an additional safety measure, the plasma is tested with Nucleic Acid Tests (NATs) for Hepatitis A Virus (HAV), Hepatitis B Virus (HBV), HCV and HIV-1 and found to be non-reactive (negative). The plasma is also screened for Human Parvovirus (B19V) by NAT. The limit for B19V DNA in the mini-pool is set not to exceed 10 ^3 IU/mL. Only plasma that passed virus screening is used for production.

The FIBRYGA manufacturing process includes a solvent/detergent (S/D) step for virus inactivation, and a nanofiltration step (Planova 20N nanofilter or Pegasus SV4 nanofilter) for virus removal. The mean cumulative virus reduction factors of these steps are summarized in Table 2 below.

Table 2: Cumulative Virus Reduction Factors (Log 10) During FIBRYGA Manufacture

PRV: Pseudorabies Virus, model for large enveloped DNA viruses

BVDV: Bovine Virus Diarrhea Virus, model for HCV

PPV: Porcine Parvovirus, model for B19V

n.a.: not applicable

* When the nanofiltration step was performed using a Pegasus SV4 nanofilter, the virus reduction factors for HIV-1, PRV, BVDV, HAV, and PPV were ≥ 3.9, ≥ 6.3, ≥ 5.0, ≥ 5.2, and 4.5, respectively. The cumulative virus reduction factors (S/D treatment + Pegasus SV4 nanofiltration) were ≥ 9.0, ≥ 12.9, ≥ 10.8, ≥ 5.2, and 4.5, respectively.

12 CLINICAL PHARMACOLOGY

12.1 Mechanism of Action

Fibrinogen (Factor I) is a soluble plasma protein that, during the coagulation process, is converted to fibrin, one of the key components of the blood clot. Fibrinogen is a heterohexamer with a molecular weight of 340 kDa and composed of two sets of A alpha , B beta , and gamma polypeptide chains.

Following coagulation activation and thrombin generation, fibrinogen is cleaved by thrombin at specific sites on the A alpha and B beta chains to remove fibrinopeptide A (FPA) and fibrinopeptide B (FPB). The removal of FPA and FPB exposes binding sites on the fibrinogen molecule and leads to the formation of fibrin monomers that subsequently undergo polymerization. The resulting fibrin is stabilized by activated factor XIII. Factor XIIIa acts on fibrin to form cross links between fibrin polymers and renders the fibrin clot more resistant to fibrinolysis. The end product of the coagulation cascade is cross-linked fibrin which stabilizes the primary platelet plug and achieves secondary hemostasis.

12.2 Pharmacodynamics

Administration of FIBRYGA to patients with congenital fibrinogen deficiency supplements the missing coagulation factor or increases low plasma fibrinogen levels. Normal plasma fibrinogen level is in the range of 200-450 mg/dL.

An open-label, prospective, randomized, controlled, two-arm, cross-over study was conducted in 22 patients with congenital fibrinogen deficiency (afibrinogenemia), ranging in age from 12 to 53 years (6 adolescents, 16 adults). Each patient received a single intravenous 70 mg/kg dose of FIBRYGA and the comparator product. Blood samples were drawn from the patients to measure the fibrinogen activity at baseline and up to 14 days after the infusion. Maximum Clot Firmness (MCF) was measured by thromboelastometry (ROTEM).

For each patient, MCF was determined before (baseline) and one hour after the single dose administration of FIBRYGA. In this cross-over study, the results were compared with another fibrinogen concentrate available on the US market. The results of the study demonstrated that the MCF values were significantly higher after administration of FIBRYGA than at baseline (see Table 3). The mean change from pre-infusion to 1 hour post-infusion was 9.7 mm in the primary analysis (9.0 mm for patients < 18 years old and 9.9 mm for patients ≥ 18 to < 65 years old).

Table 3: MCF [mm] (ITT population) n=22

Time point | Mean ± SD | Median (range)
Pre-infusion | 0 ± 0 | 0 (0-0)
1 hour post-infusion | 9.7 ± 3.0 | 10.0 (4.0-16.0)
Mean change (primary analysis) a | 9.7 ± 3.0 | 10.0 (4.0-16.0)

MCF = maximum clot firmness; mm = millimeter; ITT = intention-to-treat.

a p-value was <0.0001, 95% CI 8.37, 10.99

12.3 Pharmacokinetics

An open-label, prospective, randomized, controlled, two-arm, cross-over study was conducted in 22 patients with congenital fibrinogen deficiency (afibrinogenemia), ranging in age from 12 to 53 years (6 adolescents, 16 adults), where each patient received a single intravenous 70 mg/kg dose of FIBRYGA and the comparator product . In addition, a prospective, open-label, uncontrolled, multicenter clinical study was conducted in 14 pediatric patients with afibrinogenemia, ranging in age from 1 to 10 years. Thirteen patients each received a single intravenous 70 mg/kg dose of FIBRYGA. In both studies, blood samples were drawn from the patients to determine the fibrinogen activity at baseline and up to 14 days after the infusion. The pharmacokinetic parameters of FIBRYGA (n=34) are summarized in Table 4.

In the study of adult and adolescent patients, the incremental in vivo recovery (IVR) was determined from levels obtained up to 4 hours post-infusion. The median incremental IVR was a 1.8 mg/dL (range 1.1-2.6 mg/dL) increase per mg/kg. The median in vivo recovery indicates that a dose of 70 mg/kg will increase patients’ fibrinogen plasma concentration by approximately 125 mg/dL. In pediatric patients, the incremental in vivo recovery (IVR) was determined from levels obtained up to 3 hours post-infusion. The median incremental IVR was a 1.4 mg/dL (range 1.3-2.1 mg/dL) increase per mg/kg.

Table 4: Pharmacokinetic Parameters for Fibrinogen Activity

C max = maximum plasma concentration; AUC = area under the curve; AUC norm = area under the curve normalized to the dose administered; SD = standard deviation

No difference in fibrinogen activity was observed between males and females. There was no difference in the pharmacokinetics of FIBRYGA between adults and adolescents (12-17 years of age). Lower recovery, shorter half-life and faster clearance were observed in children aged 1 to < 12 years, compared to adults and adolescents. Other parameters, such as Cmax (maximum plasma concentration), AUC (area under the curve) and AUCnorm (area under the curve normalized to the dose administered), were also lower in children. Such differences may be expected for the younger age subgroup owing to physiological differences in body size and composition.

14 CLINICAL STUDIES

Acquired Fibrinogen Deficiency

FIBRYGA was investigated in a prospective, multicenter, randomized, controlled, single-blinded study conducted in adult cardiac surgical patients for whom fibrinogen supplementation was ordered in accordance with accepted clinical standards (significant hemorrhage and known or presumed hypofibrinogenemia). A total of 195 patients 17–65 years of age were included in the FIBRYGA group and 203 in the cryoprecipitate group. There were 177 patients >65 years of age included in the FIBRYGA group and 160 in the cryoprecipitate group. A pre-planned interim analysis was conducted based on 302 in the FIBRYGA group and 303 in the cryoprecipitate group.

Hypofibrinogenemia was defined as a plasma fibrinogen level <2.0 g/L by the Clauss method or by clot amplitude at 10 minutes of the fibrin-based clot <10 mm by thromboelastometry. Patients were randomly assigned to receive either FIBRYGA, 4 g infused over approximately 10 minutes (infusion rate 20 mL per minute), or cryoprecipitate, 10 units infused according to local practice. The doses were to be repeated as needed.

Patients received a median of 4 g (range 2.0–20.0) of fibrinogen concentrate and 10 units (range 10.0–120.0) of cryoprecipitate. The fibrinogen level increased from 1.7 ± 0.6 g/L to 2.5 ± 0.6 g/L in the FIBRYGA group and from 1.7 ± 0.6 g/L to 2.3 ± 0.6 g/L for the cryoprecipitate group, representing a mean increase of 0.9 ± 0.4 g/L in the FIBRYGA group and 0.7 ± 0.4 g/L in the cryoprecipitate group.

FIBRYGA was demonstrated to be non-inferior to cryoprecipitate based on the total number of units of allogeneic blood products (ABPs) administered during the first 24 hours after termination of cardiopulmonary bypass (CPB) (see Table 5).

Table 5: Primary Outcome: Comparison of the Total Number of Allogeneic Blood Product Units Transfused Within 24 Hours After Termination of CPB

 | Mean ± SD | Median (IQR) | ABP mean ratio estimate*
FIBRYGA (n=302) | 17.0 ± 17.7 | 12.0 (6.0-23.0) | 0.98
Cryoprecipitate (n=303) | 17.4 ± 17.0 | 14.0 (6.0-23.0)

CPB = cardiopulmonary bypass; SD = standard deviation; IQR = interquartile range; ABP = allogeneic blood product; CI = confidence interval

*Using ordinary Poisson regression, the 99.742% upper CI limit was calculated to be 1.04, below the pre-specified 1.20 non-inferiority margin, demonstrating FIBRYGA was non-inferior to cryoprecipitate (p<0.0001, compared to the pre-specified alpha level of 0.00258)

Congenital Fibrinogen Deficiency

The following data come from patients with congenital fibrinogen deficiency (afibrinogenemia and hypofibrinogenemia) treated in two prospective, open-label, uncontrolled, multicenter clinical studies to assess efficacy of FIBRYGA for treatment of bleeding events (BEs), one study evaluated 24 adolescents and adults ages 12 to 54 years, and one evaluated 8 children 1 to 10 years of age.

Efficacy of FIBRYGA in treating BEs was measured using an objective 4-point hemostatic efficacy-scale based on criteria such as bleeding cessation, changes in hemoglobin, and use of any other hemostatic means. In the adult and adolescent study, 24 patients received FIBRYGA treatment for 87 evaluable BEs one of which was major and 86 minor. Major bleeding included spontaneous intracranial hemorrhage, while minor bleeding included spontaneous occult gastrointestinal bleeding, mild hemarthrosis, superficial muscle, soft tissue or oral bleeding. Sixty-five (75%) of evaluable BEs were spontaneous and 22 (25%) BEs were traumatic. The major BE (intracranial hemorrhage) required two infusions. The median number of infusions for minor BEs was one. Four (4.5%) minor BEs required 2 infusions and one (1.1%) minor BE (gastrointestinal bleeding) required 7 infusions. The treatment of one BE was classified as failure (moderate efficacy) and 86 of 87 (98.9%) of evaluable BEs were assessed as having a successful efficacy outcome (8 ratings of good and 78 ratings of excellent efficacy).

Ten BEs were treated in the study of children, 2 were major and 8 minor. Major bleeds were thigh hematoma, and intraperitoneal bleed from splenic rupture, while minor bleeding included soft tissue or oral bleeding. Five (50.0%) BEs were spontaneous and five (50.0%) were traumatic. The median (range) number of infusions per BE was 1 (1-4). Of the two major treated BEs, one required three infusions, while the other received four infusions, both achieved a hemostatic efficacy score of good. Three of 10 BEs in children were assessed as having a good hemostatic efficacy score, and seven as having an excellent hemostatic efficacy score, therefore 10 (100%) had a successful efficacy outcome (rating of good or excellent efficacy).

16 HOW SUPPLIED/STORAGE AND HANDLING

The following nominal dosage forms are available:

Carton NDC Number | Container (bottle) NDC Number | Size | Color coding
68982-349-01 | 68982-349-81 | 1 g Fibrinogen and 50 mL diluent | green
68982-350-01 | 68982-350-81 | 2 g Fibrinogen and 100 mL diluent | grey

- FIBRYGA is supplied in a package with a single-dose bottle of lyophilized powder and a vial of diluent (sterile Water for Injection), together with a transfer device.
- The actual potency of fibrinogen in mg is stated on each FIBRYGA carton and bottle.
- Components used in the packaging of FIBRYGA are not made with natural rubber latex.

Storage and Handling:

- Store FIBRYGA for up to 48 months at +2°C to + 25°C (36°F to 77°F) from the date of manufacture.
- Do not use FIBRYGA beyond the expiration date printed on the carton and bottle.
- Do not freeze. Store in the original container to protect from light.
- After reconstitution, do not refrigerate or freeze the FIBRYGA solution. Use the reconstituted FIBRYGA solution immediately or within 4 hours after reconstitution.
- Dispose of any unused product or waste material in accordance with local requirements.

17 PATIENT COUNSELING INFORMATION

- Inform patients of the early signs of hypersensitivity or allergic reactions to FIBRYGA, including hives, chest tightness, wheezing, hypotension, and anaphylaxis [see Warnings and Precautions (5.1)] . Advise them to notify their physician immediately if they experience any of these symptoms.

- Inform patients that blood clots with or without consequent obstruction of blood flow may occur with FIBRYGA. Any symptoms of blood clots such as unexplained chest and/or leg pain or swelling of the legs or arms, coughing up blood, shortness of breath, increased rate of breathing or unexplained symptoms related to the nervous system such as stroke or weakness following administration of FIBRYGA should be reported to their physician immediately [see Warnings and Precautions (5.2)] .

- Inform patients that FIBRYGA is made from human plasma (part of the blood) and may contain infectious agents, e.g., viruses and, theoretically, the Creutzfeldt-Jakob Disease agent, that can cause disease. Explain that the risk FIBRYGA may transmit an infectious agent has been reduced by screening the plasma donors, by testing the donated plasma for certain virus infections, and by two processes demonstrated to inactivate and/or remove certain viruses during manufacturing [see Warnings and Precautions (5.3)] . Symptoms of a possible virus infection include headache, fever, nausea, vomiting, weakness, malaise, diarrhea, or, in the case of hepatitis, jaundice.

Manufactured by:

Octapharma Pharmazeutika Produktionsges.m.b.H.

Oberlaaer Strasse 235

A-1100 Vienna, Austria

Octapharma AB

Lars Forssells gata 23

SE-112 75, Sweden

U.S. License No. 1646

Distributed by:

Octapharma USA Inc.

117 West Century Road

Paramus, NJ 07652

Instructions for Use

FIBRYGA / fye bri ' gah /

Fibrinogen (Human)

Read these instructions carefully before using FIBRYGA for the first time. The general guidelines for mixing and infusing FIBRYGA are listed below. If you are unsure of any of these steps, please contact the manufacturer before using FIBRYGA.

FIBRYGA is supplied as a powder. Before it can be infused, it must be mixed with sterile Water for Injection.

FIBRYGA is provided with the Nextaro transfer device for reconstitution of the FIBRYGA powder in sterile Water for Injection.

Instructions for Mixing FIBRYGA

1. Warm both the powder and sterile Water for Injection (sWFI) in their closed bottles to room temperature. This temperature should be maintained during reconstitution. If a water bath is used for warming, prevent water from coming into contact with the rubber stoppers or the caps of the bottles. The temperature of the water bath should not exceed +37°C (98°F).
2. Remove the flip cap from the FIBRYGA bottle and the sWFI vial and disinfect the rubber stoppers with an alcohol swab and allow to dry.
3. Open the Nextaro ® transfer device package by peeling off the lid (Fig. 1). To maintain sterility, do not remove the Nextaro ® transfer device from the blister package. Do not touch the spike.

4. Place the diluent vial on an even, clean surface and hold it firmly. Without removing the blister package, place the blue part of the transfer device on top of the diluent vial. Press straight and firmly down until it snaps into place (Fig. 2). Do not twist while attaching.
Note:
The transfer device must be attached to the diluent vial first and then to the lyophilized powder bottle. Otherwise, loss of vacuum occurs, and transfer of the diluent does not take place. If diluent is not completely transferred to the lyophilized powder bottle during this process, contact your Octapharma representative.

5. While holding onto the diluent vial, carefully remove the blister package from the Nextaro ® transfer device by pulling vertically upwards. Make sure to leave the transfer device attached firmly to the diluent vial (Fig. 3).

6. Place the FIBRYGA bottle on an even, clean surface and hold it firmly. Take the diluent vial with the attached transfer device and turn it upside down. Place the white part of the transfer device connector on top of the FIBRYGA bottle and press firmly down until it snaps into place (Fig. 4). Do not twist while attaching. The diluent will flow automatically into the FIBRYGA bottle.

7. With the diluent vial still attached, gently swirl the FIBRYGA bottle until the powder is fully dissolved. To avoid foam formation, do not shake the bottle. The powder should be dissolved completely within approximately 5-10 minutes. Unscrew the Nextaro ® transfer device (blue part) counterclockwise into two parts (Fig. 5). Do not touch the Luer lock connector on the white part of the transfer device.
8. Dispose of the empty diluent vial together with the blue part of the transfer device.

- After reconstitution, the FIBRYGA solution should be almost colorless and slightly opalescent. Inspect the reconstituted FIBRYGA solution in the syringe for visible particulate matter and discoloration prior to administration. Do not use if particulate matter or discoloration are observed.

The powder should be reconstituted only directly before injection. After reconstitution, do not refrigerate or freeze the FIBRYGA solution. Use the reconstituted FIBRYGA solution immediately or within 4 hours after reconstitution. Discard any remaining FIBRYGA solution.

Instructions for infusion

For intravenous use only after reconstitution.

1. Carefully attach a syringe to the Luer lock connector on the white part of the Nextaro ® transfer device (Fig. 6).

2. Turn the FIBRYGA bottle upside down and draw the solution into the syringe (Fig. 7).

3. Once the solution has been transferred, firmly hold the barrel of the syringe (keeping the syringe plunger facing down) and remove the syringe from the Nextaro ® transfer device (Fig. 8).
4. Dispose of the white part of the transfer device together with the empty FIBRYGA bottle.

5. Inspect the reconstituted FIBRYGA solution in the syringe for visible particulate matter and discoloration prior to administration. Do not use if particulate matter or discoloration are observed.
6. Do not administer FIBRYGA in the same tubing or container as other medications.
7. Use aseptic technique when administering FIBRYGA.
8. Clean the chosen injection site with an alcohol swab.
9. Attach a standard infusion set to the syringe. Insert the needle of the infusion set into the chosen vein. Flush the infusion line with normal saline before and after administration of FIBRYGA.
10. Perform intravenous infusion. The rate of administration should be determined by the patient’s comfort level, at a recommended maximum rate of 20 mL per minute in patients with acquired fibrinogen deficiency and 5 mL per minute in patients with congenital fibrinogen deficiency.
11. No blood should enter the syringe due to the risk of fibrin clot formation.
12. After infusing FIBRYGA, remove and properly discard the infusion set. After the infusion, remove the peel-off label containing the batch number from the FIBRYGA bottle, and place it in the log book for record keeping. Discard the empty bottle.

Manufactured by:

Octapharma Pharmazeutika Produktionsges.m.b.H.

Oberlaaer Strasse 235

A-1100 Vienna, Austria

Octapharma AB

Lars Forssells gata 23

SE-112 75, Sweden

U.S. License No. 1646

Distributed by:

Octapharma USA, Inc.

117 West Century Road

Paramus, NJ 07652

FIBRYGA is a registered trademark of Octapharma.

Issued August 2025.

PACKAGE LABEL - PRINCIPAL DISPLAY PANEL

Vial Label – Principal Display Panel

Fibryga

1g Range

NDC 68982-349-81

Fibryga

2g Range

NDC 68982-350-81

Carton Label – Principal Display Panel

Fibryga

1g Range

NDC 68982-349-01

Fibryga

2g Range

NDC 68982-350-01